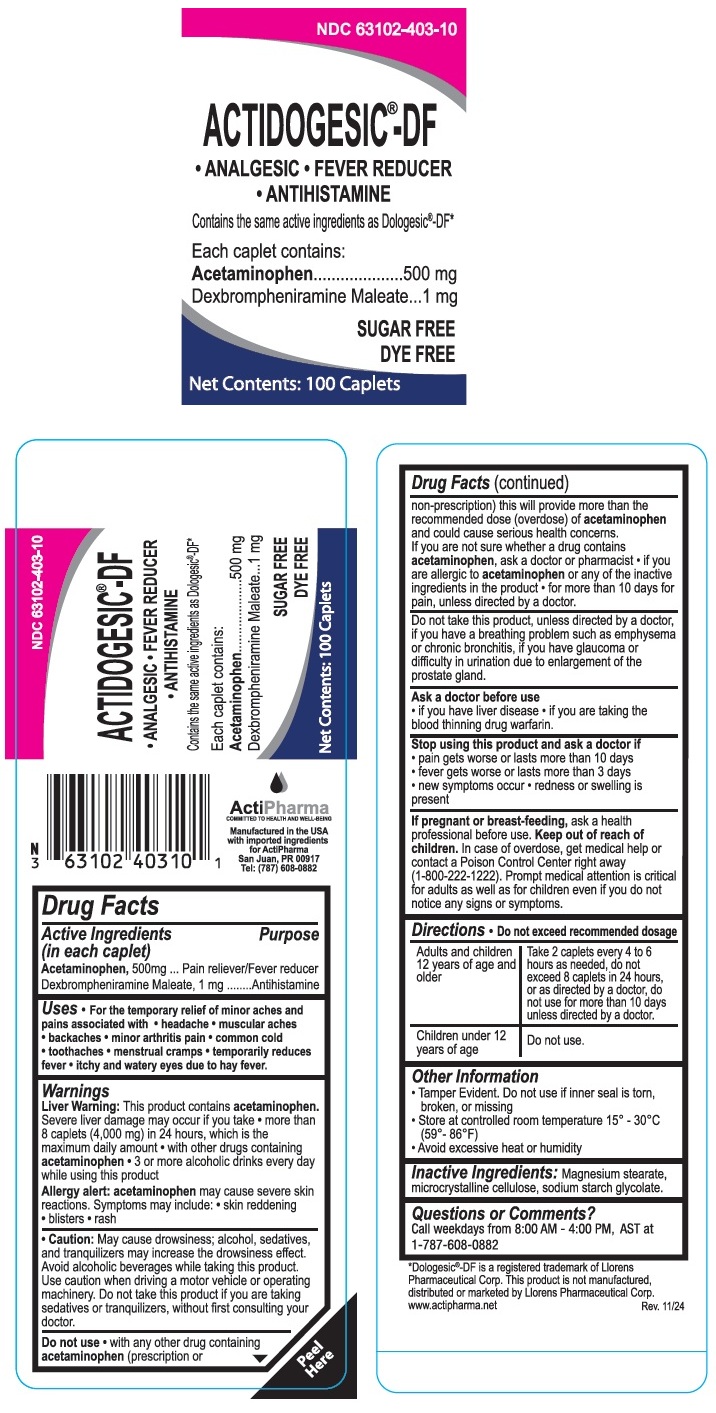 DRUG LABEL: ACTIDOGESIC DF
NDC: 63102-403 | Form: TABLET
Manufacturer: ACTIPHARMA, LLC
Category: otc | Type: HUMAN OTC DRUG LABEL
Date: 20250709

ACTIVE INGREDIENTS: ACETAMINOPHEN 500 mg/1 1; DEXBROMPHENIRAMINE MALEATE 1 mg/1 1
INACTIVE INGREDIENTS: MAGNESIUM STEARATE; MICROCRYSTALLINE CELLULOSE; SODIUM STARCH GLYCOLATE TYPE A

ACTIDOGESIC®- DF

Active Ingredients (in each caplet)

Acetaminophen, 500 mg
Dexbrompheniramine Maleate, 1 mg

Purpose

Pain reliever/Fever reducer
Antihistamine

Uses

• For the temporary relief of minor aches and pains associated with • headache • muscular aches • backaches • minor arthritis pain • common cold • toothaches • menstrual cramps • temporarily reduces fever • itchy and watery eyes due to hay fever.

Warnings

Liver Warning: This product contains acetaminophen. Severe liver damage may occur if you take • more than 8 caplets (4,000 mg) in 24 hours, which is the maximum daily amount • with other drugs containing acetaminophen • 3 or more alcoholic drinks every day while using this product

Allergy alert: acetaminophen may cause severe skin reactions. Symptoms may include: • skin reddening • blisters • rash

• Caution: May cause drowsiness; alcohol, sedatives, and tranquilizers may increase the drowsiness effect. Avoid alcoholic beverages while taking this product. Use caution when driving a motor vehicle or operating machinery. Do not take this product if you are taking sedatives or tranquilizers, without first consulting your doctor.

Do not use • with any other drug containing acetaminophen (prescription or non-prescription) this will provide more than the recommended dose (overdose) of acetaminophen and could cause serious health concerns. If you are not sure whether a drug contains acetaminophen, ask a doctor or pharmacist • if you are allergic to acetaminophen or any of the inactive ingredients in the product • for more than 10 days for pain, unless directed by a doctor.

Do not take this product, unless directed by a doctor, if you have a breathing problem such as emphysema or chronic bronchitis, if you have glaucoma or difficulty in urination due to enlargement of the prostate gland.

Ask a doctor before use

• if you have liver disease • if you are taking the blood thinning drug warfarin.

Stop using this product and ask a doctor if
• pain gets worse or lasts more than 10 days
• fever gets worse or lasts more than 3 days
• new symptoms occur • redness or swelling is present

If pregnant or breast-feeding, ask a health professional before use.

Keep out of reach of children. In case of overdose, get medical help or contact a Poison Control Center right away (1-800-222-1222). Prompt medical attention is critical for adults as well as for children even if you do not notice any signs or symptoms.

Directions

• Do not exceed recommended dosage

Adults and children; 12 years of age and; older | Take 2 caplets every 4 to 6 hours as needed,; do not exceed 8 caplets in 24 hours, or as; directed by a doctor, do not use for more than; 10 days unless directed by a doctor.
Children under 12 years of age | Do not use.

Other Information

• Tamper Evident. Do not use if inner seal is torn, broken, or missing
• Store at controlled room temperature 15°- 30°C (59°- 86°F)
• Avoid excessive heat or humidity

Inactive Ingredients:

Magnesium stearate, microcrystalline cellulose, sodium starch glycolate.

Questions or Comments?

Call weekdays from 8:00 AM - 4:00 PM, AST at 1-787-608-0882

Contains the same active ingredients as Dologesic®-DF*

SUGAR FREE

DYE FREE

ActiPharma
COMMITTED TO HEALTH AND WELL-BEING

Manufactured in the USA with imported ingredients for ActiPharma San Juan, PR 00917 Tel: (787) 608-0882

*Dologesic®-DF is a registered trademark of Llorens Pharmaceutical Corp. This product is not manufactured, distributed or marketed by Llorens Pharmaceutical Corp.
www.actipharma.net